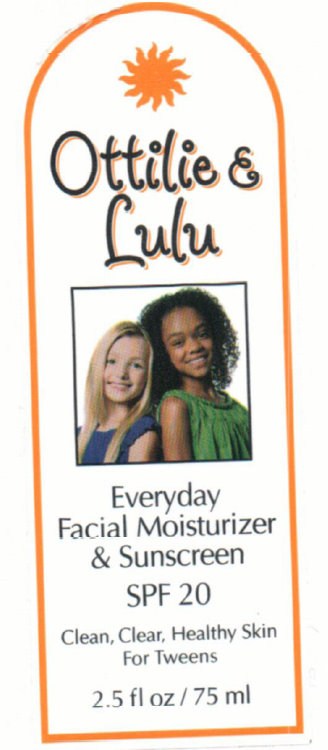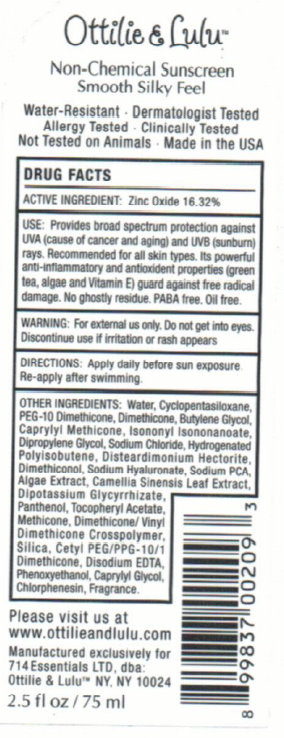 DRUG LABEL: Everyday Facial Moisturizer And Sunscreen SPF 20
NDC: 76230-727 | Form: CREAM
Manufacturer: 714 Essentials LTD
Category: otc | Type: HUMAN OTC DRUG LABEL
Date: 20231212

ACTIVE INGREDIENTS: ZINC OXIDE 163.2 mg/1 mL
INACTIVE INGREDIENTS: WATER; CYCLOMETHICONE 5; DIMETHICONE; BUTYLENE GLYCOL; ISONONYL ISONONANOATE; DIPROPYLENE GLYCOL; SODIUM CHLORIDE; HYALURONATE SODIUM; SODIUM PYRROLIDONE CARBOXYLATE; GREEN TEA LEAF; GLYCYRRHIZINATE DIPOTASSIUM; PANTHENOL; SILICON DIOXIDE; EDETATE DISODIUM; PHENOXYETHANOL; CAPRYLYL GLYCOL; CHLORPHENESIN

Everyday Facial Moisturizer And Sunscreen SPF 20

ACTIVE INGREDIENT: Zinc Oxide 16.32%

Purpose

Sunscreen

INDICATIONS AND USAGE

USE: Provides broad spectrum protection against UVA (cause of cancer and aging) and UVB (sunburn) rays. Recommended for all skin types. Its powerful anti-inflammatory and antioxident properties (green tea, algae, and Vitamin E) guard against free radical damage. No ghostly residue. PABA free. Oil free.

WARNING:

For external us only. Do not get into eyes.

Discontinue use if irritation or rash appears.

Keep out of childrens reach

DOSAGE AND ADMINISTRATION

DIRECTIONS: Apply daily before sun exposure Re-apply after swimming.

OTHER INGREDIENTS:

Water, Cyclopentasiloxane, PEG-10 Dimethicone, Dimethicone, Butylene Glycol, Caprylyl Methicone, Isononyl Isononanoate, Dipropylene Glycol, Sodium Chloride, Hydrogenated Polyisobutene, Disteardimonium Hectorite, Dimethiconol, Sodium Hyaluronate, Sodium PCA, Algae Extract, Camellia Sinensis Leaf Extract, Dipotassium Glycyrrhizate, Panthenol, Tocopheryl Acetate, Methicone, Dimethicone/Vinyl Dimethicone Crosspolymer, Silica, Cetyl PEG/PPG-10/1 Dimethicone, Disodium EDTA, Phenoxyethanol, Caprylyl Glycol, Chlorphenesin, Fragrance.

DESCRIPTION

Ottilie and Lulu Non-Chemical Sunscreen Smooth Silky Feel Water-Resistant - Dermatologist Tested Allergy Tested - Clinically Tested Not Tested on Animals - Made in the USA Please Visit us at www.ottilieandlulu.com Manufactured exclusively for 714 Essentials LTD. Dba: Ottilie and Lulu'" NY. NY 10024

PACKAGE LABEL

Ottilie and Lulu Everyday Facial Moisturizer And Sunscreen SPF 20 Clean, Clear, Healthy Skin For Tweens 2.5 fl oz / 75 ml

PACKAGE LABEL

Please Visit us at www.ottilieandlulu.com Manufactured exclusively for 714 Essentials LTD. Dba: Ottilie and Lulu'" NY. NY 10024 2.5 fl oz / 75 ml 8 99837 00209 3